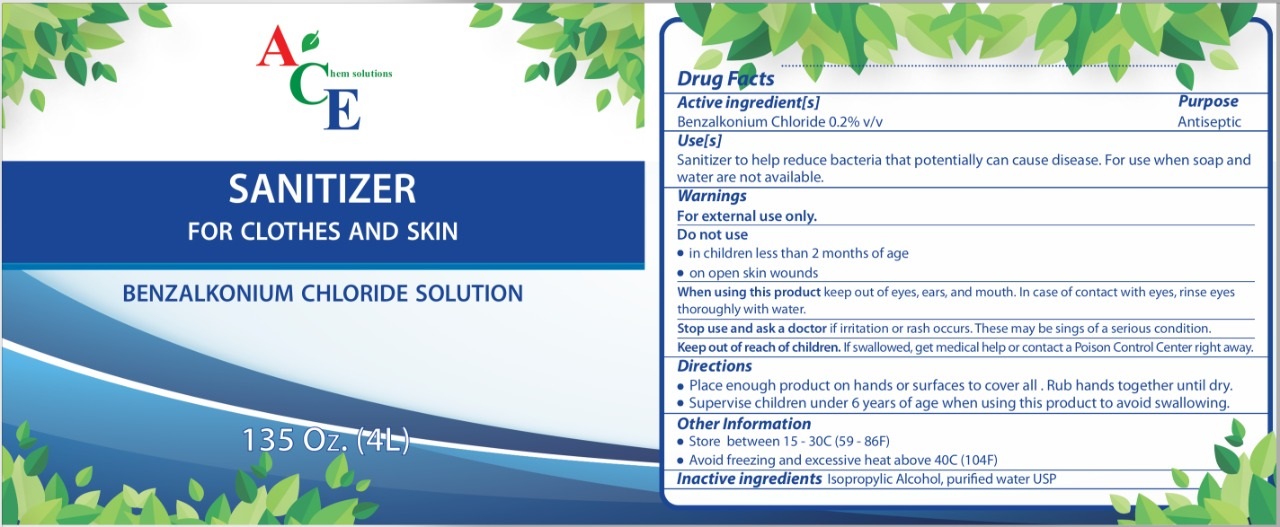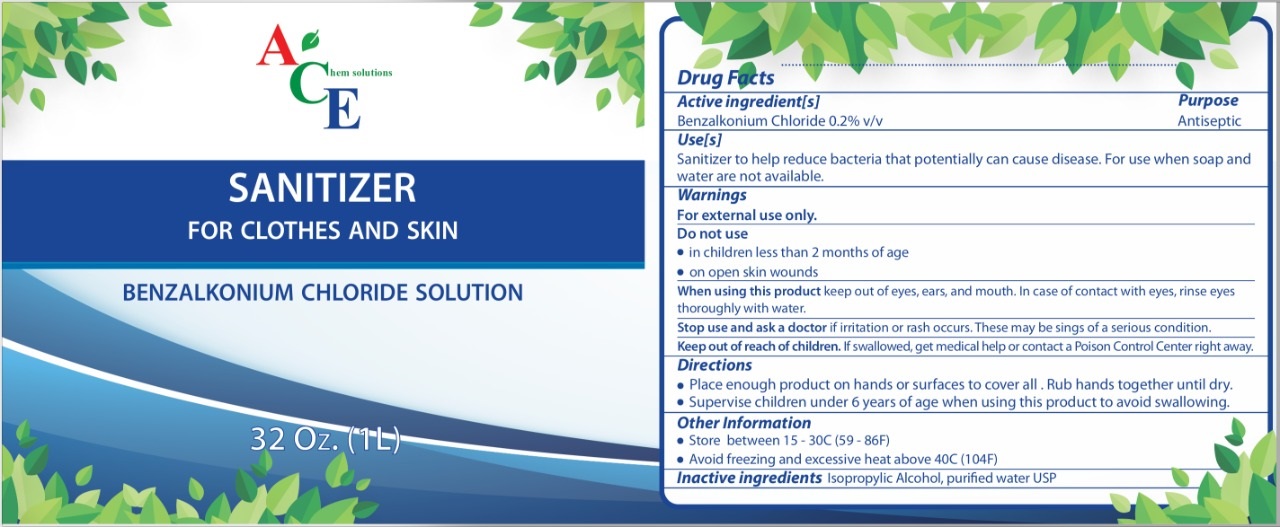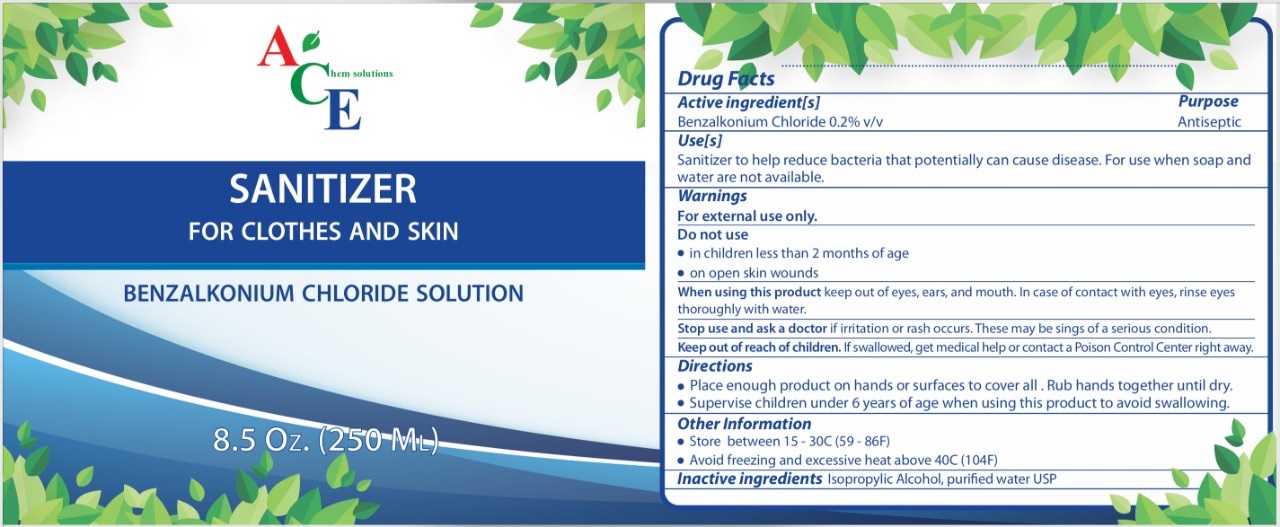 DRUG LABEL: SANITIZER
NDC: 77308-003 | Form: LIQUID
Manufacturer: ACE CHEM SOLUTIONS
Category: otc | Type: HUMAN OTC DRUG LABEL
Date: 20200628

ACTIVE INGREDIENTS: BENZALKONIUM CHLORIDE 2 g/1 L
INACTIVE INGREDIENTS: ISOPROPYL ALCOHOL 0.1 L/1 L; WATER 0.899 L/1 L

This sanitizer is manufactured using only the following United States Pharmacopoei (USP) grade ingredients in the preparation of the product (percentage in the final product formulation) consistent with World Health Organization (WHO):

Belzankonium Chloride (0.2% volume/volume (v/v)) in an aqueous solution).

Alcohol (isopropylic alcohol) (10% v/v)

Sterile distilled water or boiled cold water.

This firm does not add other active or inactive ingredients. Different or additional ingredients may impact the quality and potency of the product.

ACTIVE INGREDIENT

Benzalkonium Chloride. Purpose: Antiseptic

PURPOSE

Antiseptic, Hands, Surface and Cloths Sanitizer.

INDICATIONS AND USAGE

Sanitizer to help reduce bacteria that potentially can cause disease. For use when soap and water ar not available.

WARNINGS

For external use only.

DO NOT USE

in children less than 2 months of age

on open skin wounds

When using this product keep out eyes, ears, mouth. In case of contact with eyes, rinse eyes thoroughly with water.

Stop use and ask a doctor if irritation or rash occurs. These may be signs of a serious condition.

Keep out of reach of children. If swallowed, get medical help or contact a Poison Control Center right away.

Stop use and ask a doctor if irritation or rash occurs. These may be signs of a serious conditions.

Keep out of reach of children. If swallowed, get medical help or contact a Poison Control Center right away.

DOSAGE AND ADMINISTRATION

Place enough product on hands or surfaces to cover all. Rub hands together untill dry.

Supervise children under 6 years of age when using this products to avoid swallowing.

STORAGE AND HANDLING

Store between 15-30C (59-86F)

Avoiding freezing and excessive heat above 40C (104F)

INACTIVE INGREDIENT

Isopropylic Alcohol, purified water USP.

PACKAGE LABEL

250 ml NDC: 77308-003-01

1 L NDC: 77308-003-03

4 L NDC: 77308-003-04